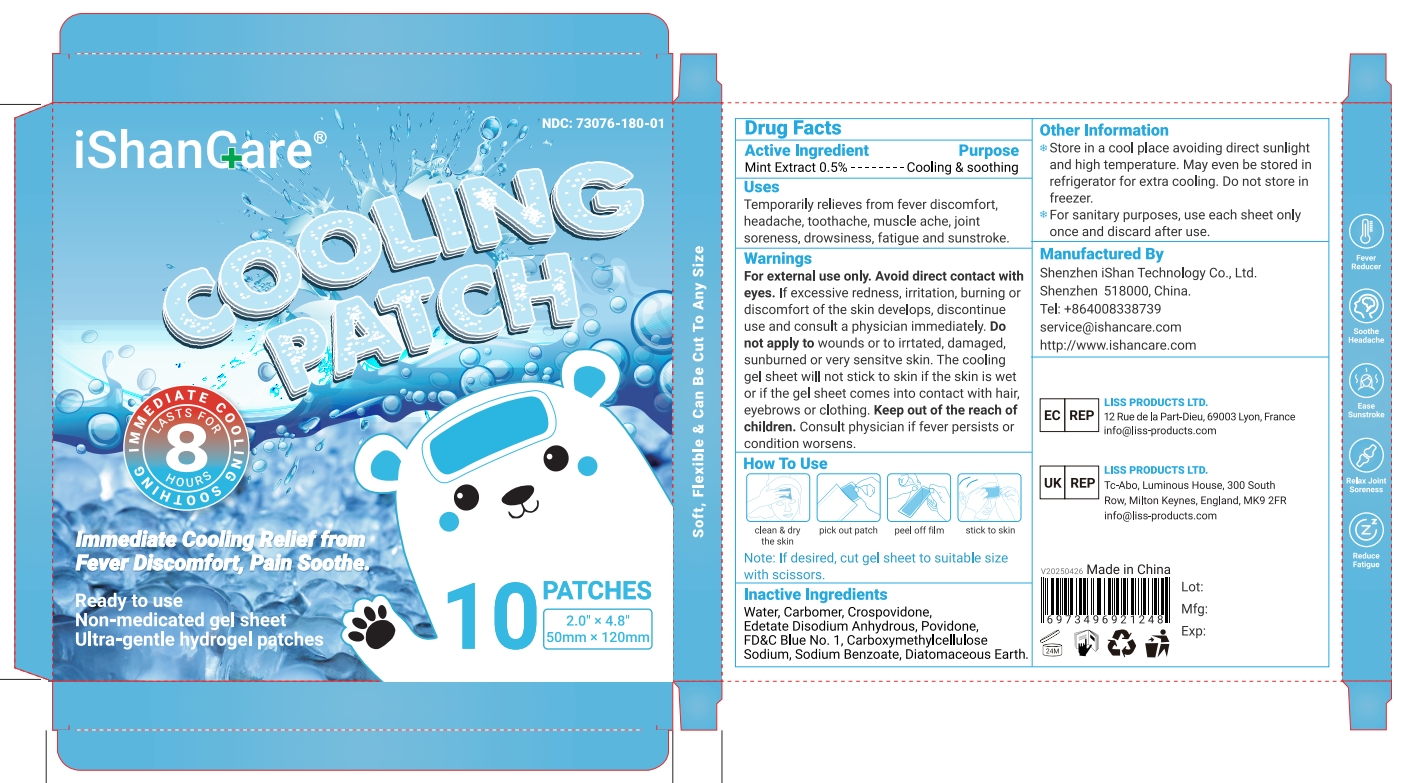 DRUG LABEL: iShanCare
NDC: 73076-180 | Form: PATCH
Manufacturer: Shenzhen Ishan Technology Co., Ltd
Category: homeopathic | Type: HUMAN OTC DRUG LABEL
Date: 20260212

ACTIVE INGREDIENTS: MINT 0.5 g/100 g
INACTIVE INGREDIENTS: CARBOMER 940; CROSPOVIDONE; EDETATE DISODIUM; POVIDONE; FD&C BLUE NO. 1; CARBOXYMETHYLCELLULOSE SODIUM; SODIUM BENZOATE; WATER; DIATOMACEOUS EARTH

Active ingredient

Mint Extract 0.5%

Inactive ingredient

Water, Carbomer, Crospovidone,Edetate Disodium Anhydrous, Povidone.FD&C Blue No.1,CarboxymethylcelluloseSodium,Sodium Benzoate, Diatomaceous Earth.

Keep out of reach of children.

if swallowed, call poison control or seek medical help.

Stop use and ask a doctor if

pain worsens or persists, or if youexperience any of these symptoms: burning, itching, rash, or other changes in theskin where the product was placed.

USES

Temporarily relieves from fever discomfort, headache, toothache, muscle ache, jointsoreness, drowsiness, fatigue and sunstroke.

Other information

Store in a cool place avoiding direct sunlightand high temperature. May even be stored inrefrigerator for extra cooling. Do not store infreezer.

For sanitary purposes, use each sheet onlyonce and discard after use.

Directions

Clean and dry the skin

Pick out patch

Peel off film

Stick to skin

Note: lf desired, cut gel sheet to suitable sizewith scissors.

Dosage & administration

Apply as needed, do not re-use.

When using this product

Do not wear this product directly on skin.

Be aware of low-temperature burns.

Warning

For external use only. Avoid direct contact witheyes.lf excessive redness, irritation, burning ordiscomfort of the skin develops, discontinueuse and consult a physician immediately. Donot apply to wounds or to irrtated, damaged,sunburned or very sensitve skin. The coolinggel sheet will not stick to skin if the skin is wetor if the gel sheet comes into contact with haireyebrows or clothing. Keep out of the reach ofchildren.Consult physician if fever persists orcondition worsens.

RECENT MAJOR CHANGES

no